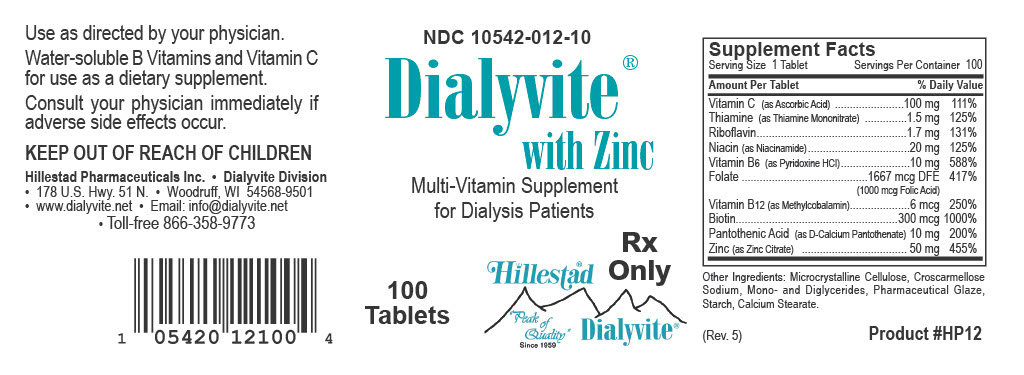 DRUG LABEL: Dialyvite with Zinc
                
NDC: 10542-012 | Form: TABLET, COATED
Manufacturer: Hillestad Pharmaceuticals USA
Category: prescription | Type: HUMAN PRESCRIPTION DRUG LABEL
Date: 20260127

ACTIVE INGREDIENTS: Ascorbic Acid 100 mg/1 1; Thiamine Mononitrate 1.5 mg/1 1; Riboflavin 1.7 mg/1 1; Niacinamide 20 mg/1 1; Pyridoxine Hydrochloride 10 mg/1 1; Folic Acid 1 mg/1 1; Cobalamin 6 ug/1 1; Biotin 300 ug/1 1; Calcium Pantothenate 10 mg/1 1; Zinc Citrate 50 mg/1 1
INACTIVE INGREDIENTS: Microcrystalline Cellulose; Croscarmellose Sodium; Glyceryl Monostearate; Shellac; Starch, Corn; Calcium Stearate

Dialyvite with Zinc

DESCRIPTION

Dialyvite with Zinc is a prescription folic acid supplement with zinc and additional nutrients for kidney dialysis patients. Dialyvite with Zinc is a small, round, yellow, clear-coated tablet, with debossed "H" on one side.

Each tablet contains:

Folic Acid.....1 mg

Vitamin C (Ascorbic Acid).....100 mg

Thiamine (Thiamine Mononitrate).....1.5 mg

Riboflavin.....1.7 mg

Niacinamide.....20 mg

Vitamin B6 (Pyridoxine HCl).....10 mg

Vitamin B12 (Methylcobalamin).....6 mcg

Biotin.....300 mcg

Pantothenic Acid (Calcium Pantothenate).....10 mg

Zinc (Zinc Citrate).....50 mg

Inactive ingredients:

Microcrystalline Cellulose, Croscarmellose Sodium, Mono-and Diglycerides, Pharmaceutical Glaze, Starch, Calcium Stearate.

INDICATIONS AND USAGE

Dialyvite with Zinc is a prescription folic acid supplement with Zinc and additional nutrients indicated for use in improving the nutritional status of renal dialysis patients.

CONTRAINDICATIONS

This product is contraindicated in patients with known hypersensitivity to any of the ingredients.

PRECAUTIONS

Folic acid supplementation may obscure pernicious anemia, in that hematologic remission can occur while neurological manifestations progress.

Keep out of reach of children.

ADVERSE REACTIONS

Allergic sensitizations have been reported following oral administration of folic acid.

Consult your physician immediately if adverse side effects occur.

DOSAGE AND ADMINISTRATION

Take one tablet per day or as directed by your physician, orally.

PRINCIPAL DISPLAY PANEL

NDC 10542-012-10

Dialyvite with Zinc

Multivitamin Supplement for Dialysis Patients

100 Tablets